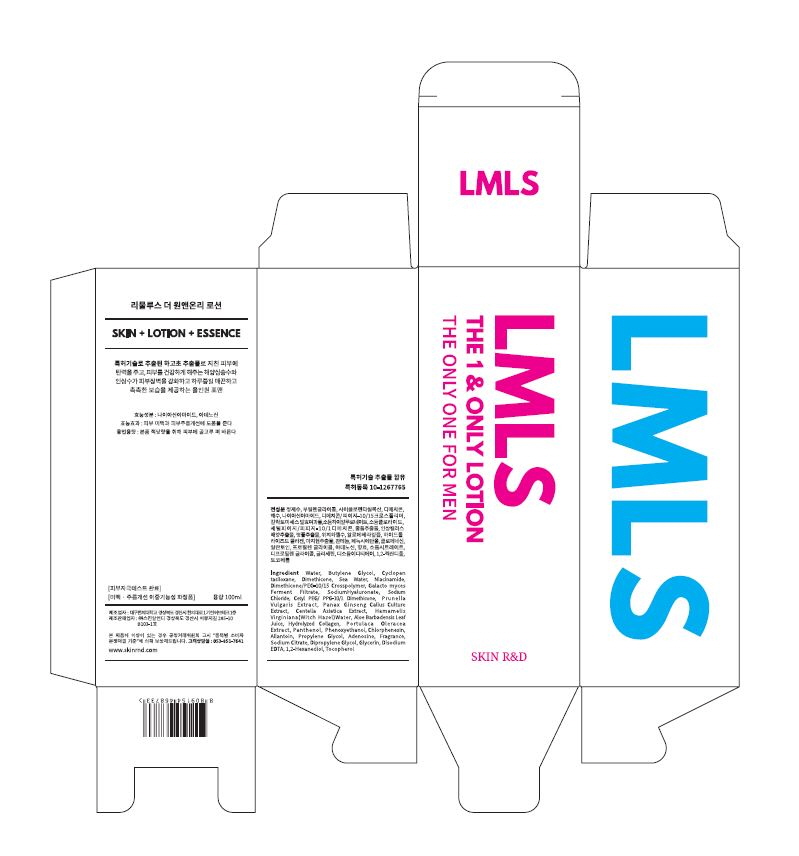 DRUG LABEL: Limulus The 1 and Only
NDC: 71464-0003 | Form: LOTION
Manufacturer: Skin R&D
Category: otc | Type: HUMAN OTC DRUG LABEL
Date: 20170703

ACTIVE INGREDIENTS: ADENOSINE 0.04 g/100 mL; NIACINAMIDE 2 g/100 mL
INACTIVE INGREDIENTS: WATER; GLYCERIN

Drug Facts

ACTIVE INGREDIENT

niacinamide, adenosine

INACTIVE INGREDIENT

Water
Butylene Glycol
Cyclopentasiloxane
Dimethicone
Dimethicone/PEG-10/15 Crosspolymer
Dipropylene Glycol
Sodium Citrate
Tocopherol
Sea Water
Butylene Glycol
Dimethicone
Niacinamide
Sodium Chloride
Galactomyces Ferment Filtrate
Panax Ginseng Callus Extract
Glycerin
1,2-Hexanediol
Prunella Vulgaris Extract
Hamamelis Virginiana (Witch Hazel) Water
Propylene Glycol
Centella Asiatica (Centella) Extract
Portulaca Oleracea Extract
Phenoxyethanol
Aloe Barbadensis Leaf Juice
Hydrolyzed Collagen
Phenoxyethanol
Cetyl PEG/PPG-10/1 Dimethicone
Chlorphenesin
Allantoin
Fragrance
Panthenol
Adenosine
Disodium EDTA
Sodium Hyaluronate

PURPOSE

Skin brightening + Anti-wrinkle

keep out of reach of the children

INDICATIONS AND USAGE

Take an appropriate amount to the skin

WARNINGS

Precautions for Use

1. Consult with a medical specialist if any abnormal symptoms or side effects, such as red spots, swelling, or itching, occur during the use of this product.

2. Do not use the product on wounded areas.

3. Precautions for storage and handling

1) Keep out of reach of children.

2) Store away from direct sunlight.

DOSAGE AND ADMINISTRATION

for external use only